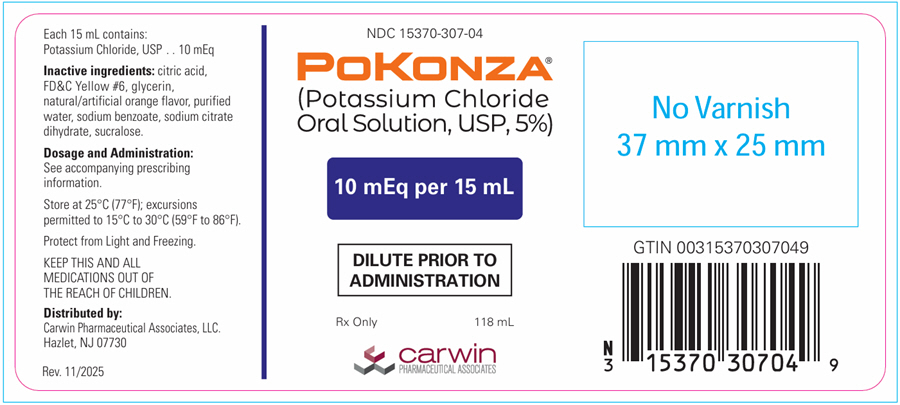 DRUG LABEL: POKONZA potassium chloride
NDC: 15370-307 | Form: LIQUID
Manufacturer: Carwin Pharmaceutical Associates, LLC
Category: prescription | Type: HUMAN PRESCRIPTION DRUG LABEL
Date: 20260122

ACTIVE INGREDIENTS: POTASSIUM CHLORIDE 10 meq/15 mL
INACTIVE INGREDIENTS: ANHYDROUS CITRIC ACID; FD&C YELLOW NO. 6; GLYCERIN; SODIUM BENZOATE; SODIUM CITRATE, UNSPECIFIED FORM; SUCRALOSE; WATER

HIGHLIGHTS OF PRESCRIBING INFORMATION

These highlights do not include all the information needed to use POKONZA® safely and effectively. See full prescribing information for POKONZA®.
POKONZA® (Potassium chloride oral solution)
Initial U.S. Approval: 1948

1 INDICATIONS AND USAGE

POKONZA® (Potassium Chloride Oral Solution, USP) is indicated for the treatment and prophylaxis of hypokalemia with or without metabolic alkalosis, in patients for whom dietary management with potassium-rich foods or diuretic dose reduction are insufficient. (1)

2 DOSAGE AND ADMINISTRATION

Dilute prior to administration. (2.1, 5.1)

Monitor serum potassium and adjust dosage accordingly (2.2, 2.3)

Treatment of hypokalemia:

- Adults: Initial doses range from 40 mEq to 100 mEq/day orally in 2 to 5 divided doses: limit doses to 40 mEq per dose. Total daily dose should not exceed 200 mEq (2.2)
- Pediatric patients aged birth to 16 years old: 2 mEq to 4 mEq/kg/day orally in divided doses; not to exceed 1 mEq/kg as a single dose or 40 mEq whichever is lower; if deficits are severe or ongoing losses are great, consider intravenous therapy. Total daily dose should not exceed 100 mEq (2.3)

Maintenance or Prophylaxis of hypokalemia:

- Adults: Typical dose is 20 mEq orally per day (2.2)
- Pediatric patients aged birth to 16 years old: typical dose is 1 mEq/kg/day orally. Do not exceed 3 mEq/kg/day (2.3)

3 DOSAGE FORMS AND STRENGTHS

- Oral Solution: 5%; 10 mEq/15mL potassium per mL (3)

4 CONTRAINDICATIONS

- Concomitant use with potassium sparing diuretics. (4)

5 WARNINGS AND PRECAUTIONS

- Gastrointestinal Irritation: Dilute before use, take with meals (5.1)

6 ADVERSE REACTIONS

Most common adverse reactions are nausea, vomiting, flatulence, abdominal pain/discomfort, and diarrhea. (6)

To report SUSPECTED ADVERSE REACTIONS, contact Carwin Pharmaceutical Associates at 1-844-700-5011 or FDA at 1-800-FDA-1088 or www.fda.gov/medwatch.

7 DRUG INTERACTIONS

- Potassium sparing diuretics: Avoid concomitant use (7.1)
- Renin-angiotensin-aldosterone inhibitors: Monitor for hyperkalemia (7.2)
- Nonsteroidal Anti-Inflammatory drugs: Monitor for hyperkalemia (7.3)

8 USE IN SPECIFIC POPULATIONS

Cirrhosis: Initiate therapy at the low end of the dosing range (8.6)

Renal Impairment: Initiate therapy at the low end of the dosing range (8.7)

FULL PRESCRIBING INFORMATION

1 INDICATIONS AND USAGE

POKONZA® (Potassium Chloride Oral Solution, USP) is indicated for the treatment and prophylaxis of hypokalemia with or without metabolic alkalosis, in patients for whom dietary management with potassium-rich foods or diuretic dose reduction are insufficient.

2 DOSAGE AND ADMINISTRATION

2.1 Administration and Monitoring

Monitoring

Monitor serum potassium and adjust dosages accordingly. For treatment of hypokalemia, monitor potassium levels daily or more often depending on the severity of hypokalemia until they return to normal. Monitor potassium levels monthly to biannually for maintenance or prophylaxis.

The treatment of potassium depletion, particularly in the presence of cardiac disease, renal disease, or acidosis requires careful attention to acid-base balance, volume status, electrolytes, including magnesium, sodium, chloride, phosphate, and calcium, electrocardiograms and the clinical status of the patient. Correct volume status, acid-base balance and electrolyte deficits as appropriate.

Administration

Dilute POKONZA® with at least 4 ounces of cold water [see Warnings and Precautions (5.1)]. Instruct patients or caregivers to use an oral dosing cup or syringe to correctly measure the prescribed amount of medication. Inform patients that oral dosing cups or syringes may be obtained from their pharmacy.

Take with meals or immediately after eating.

If serum potassium concentration is <2.5 mEq/L, use intravenous potassium instead of oral supplementation.

2.2 Adult Dosing

Treatment of hypokalemia

Daily dose range from 40 mEq to 100 mEq orally. Give in 2 to 5 divided doses; limit doses to 40 mEq per dose. The total daily dose should not exceed 200 mEq in a 24 hour period.

Maintenance or Prophylaxis

Typical dose is 20 mEq per day orally. Individualize dose based upon serum potassium levels.

Studies support the use of potassium replacement in digitalis toxicity. When alkalosis is present, normokalemia and hyperkalemia may obscure a total potassium deficit. The advisability of use of potassium replacement in the setting of hyperkalemia is uncertain.

2.3 Pediatric Dosing

Treatment of hypokalemia

Pediatric patients aged birth to 16 years old: The initial dose is 2 mEq/kg/day to 4 mEq/kg/day orally in divided doses; do not exceed as a single dose 1 mEq/kg or 40 mEq orally, whichever is lower; maximum daily doses should not exceed 100 mEq orally. If deficits are severe or ongoing losses are great, consider intravenous therapy.

Maintenance or Prophylaxis

Pediatric patients aged birth to 16 years old: Typical dose is 1 mEq/kg/day orally. Do not exceed 3 mEq/kg/day.

3 DOSAGE FORMS AND STRENGTHS

Oral Solution 5%: 10 mEq/15 mL

4 CONTRAINDICATIONS

POKONZA® is contraindicated in patients on potassium sparing diuretics.

5 WARNINGS AND PRECAUTIONS

5.1 Gastrointestinal Irritation

May cause gastrointestinal irritation if administered undiluted. Increased dilution of the solution and taking with meals may reduce gastrointestinal irritation [see Dosage and Administration (2.1)].

6 ADVERSE REACTIONS

The most common adverse reactions to oral potassium salts are nausea, vomiting, flatulence, abdominal pain/discomfort, and diarrhea.

7 DRUG INTERACTIONS

7.1 Potassium-Sparing Diuretics

Use with potassium-sparing diuretics can produce severe hyperkalemia. Avoid concomitant use.

7.2 Renin-Angiotensin-Aldosterone System Inhibitors

Drugs that inhibit the renin-angiotensin-aldosterone system (RAAS) including angiotensin converting enzyme (ACE) inhibitors, angiotensin receptor blockers (ARBs), spironolactone, eplerenone, or aliskiren produce potassium retention by inhibiting aldosterone production. Closely monitor potassium in patients receiving concomitant RAAS therapy.

7.3 Nonsteroidal Anti-Inflammatory Drugs (NSAIDs)

NSAIDs may produce potassium retention by reducing renal synthesis of prostaglandin E and impairing the renin-angiotensin system. Closely monitor potassium in patients on concomitant NSAIDs.

8 USE IN SPECIFIC POPULATIONS

8.1 Pregnancy

There are no human data related to use of POKONZA® during pregnancy, and animal studies have not been conducted. Potassium supplementation that does not lead to hyperkalemia is not expected to cause fetal harm.

The background risk for major birth defects and miscarriage in the indicated population is unknown. All pregnancies have a background risk of birth defect, loss, or other adverse outcomes. In the U.S. general population, the estimated background risk of major birth defects and miscarriage in clinically recognized pregnancies is 2 to 4% and 15 to 20%, respectively.

8.2 Lactation

Risk Summary

The normal potassium ion content of human milk is about 13 mEq per liter. Since potassium from oral supplements such as POKONZA® becomes part of the body potassium pool, as long as body potassium is not excessive, the contribution of potassium chloride supplementation should have little or no effect on the level in human milk.

8.4 Pediatric Use

The safety and effectiveness of POKONZA® have been demonstrated in children with diarrhea and malnutrition from birth to 16 years.

8.5 Geriatric Use

Clinical studies of POKONZA® did not include sufficient numbers of subjects aged 65 and over to determine whether they respond differently from younger subjects. Other reported clinical experience has not identified differences in responses between the elderly and younger patients. In general, dose selection for an elderly patient should be cautious, usually starting at the low end of the dosing range, reflecting the greater frequency of decreased hepatic, renal, or cardiac function, and of concomitant disease or other drug therapy.

This drug is known to be substantially excreted by the kidney, and the risk of toxic reactions to this drug may be greater in patients with impaired renal function.

Because elderly patients are more likely to have decreased renal function, care should be taken in dose selection, and it may be useful to monitor renal function.

8.6 Cirrhotics

Patients with cirrhosis should usually be started at the low end of the dosing range, and the serum potassium level should be monitored frequently. [see Clinical Pharmacology (12.3)].

8.7 Renal Impairment

Patients with renal impairment have reduced urinary excretion of potassium and are at substantially increased risk of hyperkalemia. Patients with impaired renal function, particularly if the patient is on ACE inhibitors, ARBs, or nonsteroidal anti-inflammatory drugs should usually be started at the low end of the dosing range because of the potential for development of hyperkalemia. The serum potassium level should be monitored frequently. Renal function should be assessed periodically.

10 OVERDOSAGE

10.1 Symptoms

The administration of oral potassium salts to persons with normal excretory mechanisms for potassium rarely causes serious hyperkalemia. However, if excretory mechanisms are impaired or if potassium is administered too rapidly potentially fatal hyperkalemia can result.

Hyperkalemia is usually asymptomatic and may be manifested only by an increased serum potassium concentration (6.5 mEq/L to 8.0 mEq/L) and characteristic electrocardiographic changes (peaking of T-waves, loss of P-waves, depression of S-T segment, and prolongation of the QT-interval). Late manifestations include muscle paralysis and cardiovascular collapse from cardiac arrest (9 mEq/L to 12 mEq/L).

10.2 Treatment

Treatment measures for hyperkalemia include the following:

1. Monitor closely for arrhythmias and electrolyte changes.
2. Eliminate foods and medications containing potassium and of any agents with potassium-sparing properties such as potassium-sparing diuretics, ARBs, ACE inhibitors, NSAIDs, certain nutritional supplements and many others.
3. Administer intravenous calcium gluconate if the patient is at no risk or low risk of developing digitalis toxicity.
4. Administer intravenously 300 to 500 mL/hr of 10% dextrose solution containing 10 to 20 units of crystalline insulin per 1000 mL.
5. Correct acidosis, if present, with intravenous sodium bicarbonate.
6. Use exchange resins, hemodialysis, or peritoneal dialysis.

In patients who have been stabilized on digitalis, too rapid a lowering of the serum potassium concentration can produce digitalis toxicity.

11 DESCRIPTION

Potassium Chloride is a white crystalline or colorless solid. It is soluble in water and slightly soluble in alcohol. Chemically, Potassium Chloride is K-Cl with a molecular mass of 74.55.

Oral Solution: 5%: 10 mEq/15 mL of solution contains 0.75 g of potassium chloride, USP and the following inactive ingredients: citric acid anhydrous, FD&C Yellow #6, glycerin, natural/ artificial orange flavor, purified water, sodium benzoate, sodium citrate dihydrate, sucralose.

12 CLINICAL PHARMACOLOGY

12.1 Mechanism of Action

The potassium ion (K+) is the principal intracellular cation of most body tissues. Potassium ions participate in a number of essential physiological processes including the maintenance of intracellular tonicity; the transmission of nerve impulses; the contraction of cardiac, skeletal, and smooth muscle; and the maintenance of normal renal function.

The intracellular concentration of potassium is approximately 150 mEq to 160 mEq per liter. The normal adult plasma concentration is 3.5 mEq to 5 mEq per liter. An active ion transport system maintains this gradient across the plasma membrane.

Potassium is a normal dietary constituent, and under steady-state conditions the amount of potassium absorbed from the gastrointestinal tract is equal to the amount excreted in the urine. The usual dietary intake of potassium is 50 mEq to 100 mEq per day.

12.3 Pharmacokinetics

Based on published literature, the rate of absorption and urinary excretion of potassium from KCl oral solution were higher during the first few hours after dosing relative to modified release KCl products. The bioavailability of potassium, as measured by the cumulative urinary excretion of K+ over a 24 hour post dose period, is similar for KCl solution and modified release products.

16 HOW SUPPLIED/STORAGE AND HANDLING

POKONZA® (Potassium Chloride Oral Solution, USP) is an orange solution available in one strength as follows:

5%:

10 mEq/15mL oral solution

NDC# 15370-307-04 Bottle of 118 mL

NDC# 15370-307-08 Bottle of 237 mL

NDC# 15370-307-16 Bottle of 473 mL

Storage

Store at Controlled Room Temperature, 25°C (77°F); excursions are permitted to 15°C to 30°C (59°F to 86°F).

Dispense in a tight, light-resistant container as defined in the USP.

PROTECT from LIGHT and FREEZING.

Rx only

Distributed by:
Carwin Pharmaceutical Associates, LLC.
Hazlet, NJ 07730

Revised: 11/2025

PRINCIPAL DISPLAY PANEL - 118 mL Bottle Label

NDC 15370-307-04

POKONZA®
(Potassium Chloride
Oral Solution, USP, 5%)

10 mEq per 15 mL

DILUTE PRIOR TO
ADMINISTRATION

Rx Only

118 mL

carwin
PHARMACEUTICAL ASSOCIATES